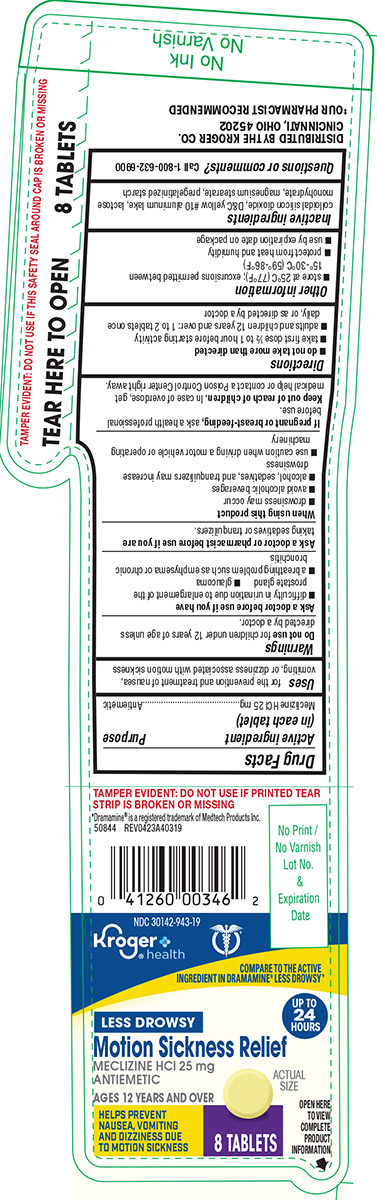 DRUG LABEL: Motion Sickness Relief
NDC: 30142-943 | Form: TABLET
Manufacturer: Kroger Company
Category: otc | Type: HUMAN OTC DRUG LABEL
Date: 20251105

ACTIVE INGREDIENTS: MECLIZINE HYDROCHLORIDE 25 mg/1 1
INACTIVE INGREDIENTS: SILICON DIOXIDE; D&C YELLOW NO. 10 ALUMINUM LAKE; LACTOSE MONOHYDRATE; MAGNESIUM STEARATE; STARCH, CORN

Kroger 44-403A

Active ingredient (in each tablet)

Meclizine HCl 25 mg

Purpose

Antiemetic

Uses

for the prevention and treatment of nausea, vomiting, or dizziness associated with motion sickness

Warnings

Do not use

for children under 12 years of age unless directed by a doctor.

Ask a doctor before use if you have

- glaucoma
- difficulty in urination due to enlargement of the prostate gland
- a breathing problem such as emphysema or chronic bronchitis

Ask a doctor or pharmacist before use if you are

taking sedatives or tranquilizers.

When using this product

- drowsiness may occur
- avoid alcoholic beverages
- alcohol, sedatives, and tranquilizers may increase drowsiness
- use caution when driving a motor vehicle or operating machinery

If pregnant or breast-feeding,

ask a health professional before use.

Keep out of reach of children.

In case of overdose, get medical help or contact a Poison Control Center right away.

Directions

- do not take more than directed
- take first dose 1/2 to 1 hour before starting activity
- adults and children 12 years and over: 1 to 2 tablets once daily, or as directed by a doctor

Other information

- store at 25°C (77°F); excursions permitted between 15°-30°C (59°-86°F)
- protect from heat and humidity
- use by expiration date on package

Inactive ingredients

colloidal silicon dioxide, D&C yellow #10 aluminum lake, lactose monohydrate, magnesium stearate, pregelatinized starch

Questions or comments?

1-800-632-6900

Principal Display Panel

COMPARE TO the active
ingredient in DRAMAMINE® LESS DROWSY*

NDC 30142-943-19

Kroger®
health

UP TO
24
Hours

Motion Sickness Relief

Meclizine HCl 25 mg
Antiemetic

AGES 12 YEARS AND OVER

HELPS PREVENT
, VOMITING
AND DIZZINESS DUE
TO MOTION SICKNESS

OPEN HERE
TO VIEW
COMPLETE
PRODUCT
INFORMATION

TAMPER EVIDENT: DO NOT USE IF PRINTED TEAR
STRIP IS BROKEN OR MISSING

*Dramamine® is a registered trademark of Medtech Products Inc.
50844 REV0423A40319

DISTRIBUTED BY THE KROGER CO.
CINCINNATI, OHIO 45202

‡OUR PHARMACIST RECOMMENDED

Kroger 44-403A